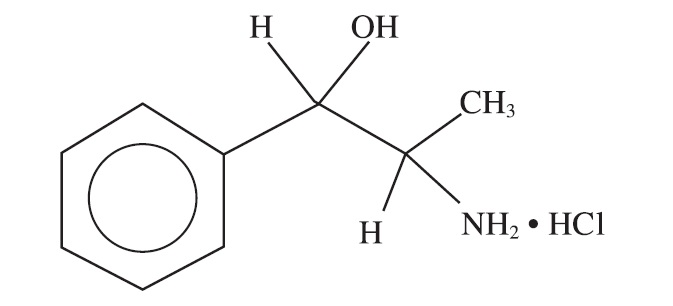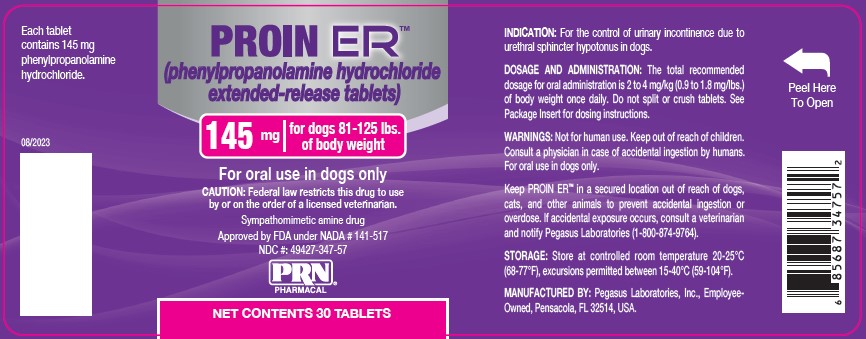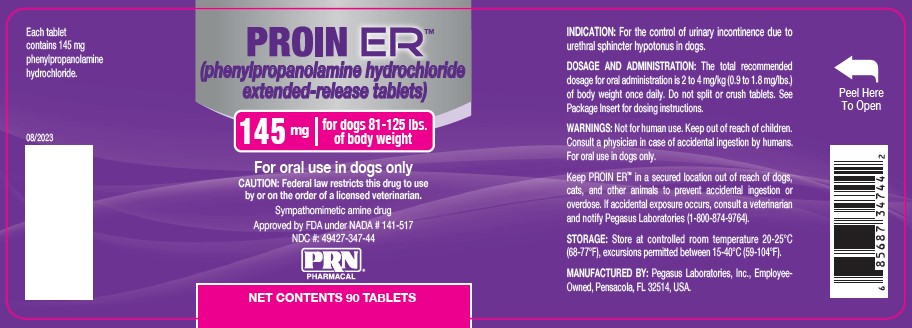 DRUG LABEL: PROIN ER
NDC: 49427-347 | Form: TABLET, EXTENDED RELEASE
Manufacturer: Pegasus Laboratories, Inc.
Category: animal | Type: PRESCRIPTION ANIMAL DRUG LABEL
Date: 20231220

ACTIVE INGREDIENTS: PHENYLPROPANOLAMINE HYDROCHLORIDE 145 mg/1 1

GENERAL PRECAUTIONS

For oral use in dogs only

CAUTION: Federal law restricts this drug to use by or on the order of a licensed veterinarian.

DESCRIPTION:

Description: PROIN ER (phenylpropanolamine hydrochloride extended-release tablets) is a sympathomimetic amine closely related to ephedrine. Phenylpropanolamine hydrochloride (PPA) is the nonproprietary designation for benzenemethanol, a-(1-aminoethyl)-hydrochloride, (R*, S*)-, (±). The empirical formula is C9H13NO•HCl and the molecular weight is 187.67. It is a white crystalline compound having a slight aromatic odor. PPA is freely soluble in water and alcohol but is practically insoluble in ether, benzene and chloroform. The chemical structure of phenylpropanolamine hydrochloride is:

INDICATION:

For the control of urinary incontinence due to urethral sphincter hypotonus in dogs.

DOSAGE AND ADMINISTRATION:

The recommended dosage is 2 to 4 mg/kg (0.9 to 1.8 mg/lb) of body weight once daily according to Table 1 below. Administer PROIN ER with food (see Clinical Pharmacology). Do not split or crush tablets.

Dogs weighing less than 10 pounds cannot be safely dosed because tablet administration would result in a dose over 4 mg/kg.

Table 1. Dose Administrationa

Body weight in pounds | PROIN ER
10-20 | 18 mg
21-40 | 38 mg
41-80 | 74 mg
81-125b | 145 mg

a Body weight should be rounded to the nearest pound.

b Dogs exceeding 125 lbs should receive the appropriate combination of tablets to achieve the recommended dosage.

Dogs may transition from PROIN® Chewable Tablets to PROIN ER without a break in administration. However, do not alternate PROIN
ER with PROIN Chewable Tablets because the effectiveness and safety of interchangeable use have not been evaluated.

WARNINGS:

Not for human use. Keep out of reach of children. Consult a physician in case of accidental ingestion by humans.

Keep PROIN ER in a secured location out of reach of dogs, cats, and other animals to prevent accidental ingestion or overdose.

PRECAUTIONS:

Proin ER may mask signs of incontinence due to urinary tract infection. PROIN ER is not effective in dogs with incontinence due to neurologic disease or malformations.

PROIN ER may cause hypertension; therefore, use with caution in dogs with pre-existing heart disease, hypertension, liver disease,
kidney insufficiency, diabetes, glaucoma, and conditions with a predilection for hypertension.

Use with caution in dogs receiving sympathomimetic drugs, tricyclic antidepressants, or monoamine oxidase inhibitors as increased toxicity
may result. Use with caution in dogs administered halogenated gaseous anesthetics as this may increase the risk of cardiac arrhythmias.

A laboratory study on human blood revealed that phenylpropanolamine (PPA) used in conjunction with aspirin may potentiate decreased platelet aggregation.^1

PROIN ER may cause increased thirst; therefore, provide dogs with ample fresh water.

The safe use of PROIN ER has not been evaluated in dogs that are intended for breeding, or that are pregnant or lactating.

ADVERSE REACTIONS:

Adverse Reactions are listed below for both PROIN ER (NADA Number 141-517) and PROIN Chewable Tablets (NADA 141-324).

PROIN ER (NADA 141-517)
In the open-label clinical study involving 119 dogs administered PROIN ER once a day for 180 days, the following adverse reactions were observed.

Table 2. Number and percentage of dogs with adverse reactions in the 180-day open-label clinical study for PROIN ER

Adverse Reactions | Total N = 119
Emesis | 39 (32.8%)
Body weight loss (≥5%) | 34 (28.6%)
Hypertension (≥160 mmHg) developed during studya | 15 (12.6%)
Diarrhea | 20 (16.8%)
Proteinuria | 16 (13.4%)
Tachycardia (≥160 bpm) | 11 (9.2%)
Lethargy | 11 (9.2%)
Decreased appetite | 10 (8.4%)
Urinary Tract Infection | 10 (8.4%)
Elevated Alkaline phosphatase and/or Alanine Aminotransferase | 7 (6.0%)
Hypoglycemia | 4 (3.3%)
Hypercalcemia | 3 (2.5%)
Increased BUN | 2 (1.7%)
Bradycardia (<60 bpm) | 2 (1.7%)
Seizures/twitching | 2 (1.7%)

a There were an additional 21 dogs enrolled with hypertension who remained hypertensive throughout the study.

During the first week of administration of PROIN ER, 15% of dogs had reported emesis, diarrhea, or decreased appetite which improved or resolved prior to the Day 21 visit.

Four deaths occurred during the study. One dog was euthanized for pulmonary metastasis and one dog for poor quality of life due to hindlimb weakness. One dog had emesis and died at home; upon necropsy a foreign body was present in the small intestine. The fourth dog had been treated for a urinary tract infection three weeks prior to sudden death of undetermined cause.

PROIN Chewable Tablets (NADA 141-324):

Table 3 below includes the most common adverse reactions observed in the masked, placebo-controlled 28-day clinical study involving 123 PROIN Chewable Tablet-treated dogs and 61 placebo-treated dogs. In addition, one dog exhibited disorientation, nervousness, a 7.7% loss of body weight, and hypertension with proteinuria. A second dog exhibited restless behavior, lethargy, a 2.8% body weight loss, and proteinuria.

Table 3. Number and percentage of dogs with adverse reactions in the 28-day placebo-controlled clinical study for PROIN Chewable Tablets

Adverse Reactions | PROIN Treated (N=123) | Placebo Treated (N=61)
Emesis | 20.3% | 8.2%
Hypertension (≥ 160mm Hg)a | 19.5% | 14.7%
Anorexia | 16.3% | 3.3%
Body weight loss (> 5%) b | 16.1% | 6.8%
Proteinuria | 13.0% | 8.2%
Anxiety/aggression/behavior change | 9.7% | 3.2%
Diarrhea | 7.3% | 9.8%
Polydipsia | 6.5% | 9.8%
Lethargy | 5.7% | 1.6%
Musculoskeletal Disorder | 3.2% | 1.6%
Insomnia/Sleep Disorder | 2.5% | 0.0%

a One or more systolic blood pressure readings of ≥160mmHg.

b The "N" for weight loss is PROIN-treated N=118 and placebo N=59 because seven dogs did not have a final weight at the time of withdrawal from the study.

ADVERSE REACTIONS

One-hundred fifty-seven dogs continued into the 6-month open-label clinical study for PROIN Chewable Tablets. The most common adverse reactions are listed in Table 4 below. In addition, one dog exhibited progressively worsening hypertension with proteinuria. Five dogs enrolled in the study with pre-existing heart disease. Of these, one dog developed systolic failure with an unknown relation to treatment.

ADVERSE REACTIONS

Table 4: Number and percentage of dogs with adverse reactions in the 6-month open-label clinical study for PROIN Chewable Tablets

Adverse Reactions | Total N= 125
Hypertension (≥ 160 mmHg)a | 34.6%
Body Weight Loss (> 5%) | 24.8%
Emesis | 19.7%
Proteinuria | 15.3%
Anorexia | 10.2%
Diarrhea | 6.4%
Lethargy | 5.7%
Anxiety/ behavior change/ aggression | 5.7%

a Percent of dogs with systolic blood pressures of ≥ 160 mmHg on day -7 were 30.2% and on day 0 were 33.3%.

ADVERSE REACTIONS

Post Approval Experience for PROIN Chewable Tablets (2015):

The following adverse reactions are based on voluntary, post approval reporting for PROIN Chewable Tablets (2015). Not all adverse events are reported to FDA/CVM. It is not always possible to reliably estimate the adverse event frequency or establish a causal relationship to product exposure using these data. The signs reported are listed in decreasing order of reporting frequency by body system:

Gastrointestinal: Emesis, anorexia, diarrhea, hypersalivation

Behavioral: Agitation, lethargy, vocalization, confusion

General body system: Polydipsia, weight loss, weakness, fever

Respiratory: Panting

Dermatological: Erythema, piloerection

Hepatic: Elevated serum alanine aminotransferase (ALT), elevated serum alkaline phosphatase (ALP)

Neurologic: Ataxia, seizures, tremors

Renal/Urinary: Renal failure, hematuria, urinary retention

Cardiovascular: Tachycardia, hypertension, bradycardia, arrhythmias

Sensory: Ophthalmic disorders, mydriasis and eye redness

In some cases, death, including euthanasia, has been reported. Sudden death was sometimes preceded by neurologic signs, vocalization,
or collapse. A necropsy of one dog revealed subarachnoidal and intraventricular hemorrhage in the brain.

The following signs have been reported more often with a dose higher than the recommended dosage: agitation, arrhythmia, bradycardia, erythema, fever, hypersalivation, hypertension, lethargy, mydriasis, panting, piloerection, tachycardia, tremor, and urinary retention.

For a copy of the Safety Data Sheet (SDS) or to report suspected adverse drug events, contact Pegasus Laboratories at 1-800-874-9764. For additional information about adverse drug experience reporting for animal drugs, contact FDA at 1-888-FDA-VETS or www.fda.gov/reportanimalae

INFORMATION FOR DOG OWNERS:

Always follow the dosage instructions for PROIN ER provided by your veterinarian. Give PROIN ER with food and do not split or crush the tablet. Monitor your dog after giving PROIN ER to be sure all of it was consumed. If you have difficulty giving PROIN ER, contact your veterinarian.

PROIN ER may cause increased thirst; therefore, provide dogs with ample fresh water.

If you forget to give your dog a dose, then resume dosing at the next scheduled dose. Keep PROIN ER in a secured location out of reach of dogs, cats, and other animals to prevent accidental ingestion or overdose.

Contact your veterinarian immediately if the dog ingests more tablets than prescribed or if other pets ingest PROIN ER. In the case of accidental ingestion by humans, contact a physician immediately.

Contact your veterinarian if you notice restlessness, irritability, loss of appetite, the incontinence persists or worsens, or any other unusual signs.

Consult your veterinarian before administering PROIN ER with any other medications.

CLINICAL PHARMACOLOGY:

Phenylpropanolamine is a chemical analogue of the endogenous sympathomimetic amines. It is an alpha-adrenergic agent which has been reported to increase urethral tone in dogs. ^2 Its mechanism of action is not well determined, but it is believed to cause the release of norepinephrine by indirectly stimulating both the alpha and beta-adrenergic receptors of the smooth muscle to increase smooth muscle tone of the urethra, bladder neck, and the internal urethral sphincter. ^(3, 4)

In a crossover pharmacokinetic study of PROIN ER in fed and fasted dogs, post-prandial drug administration was associated with approximately a 23% increase in the maximum plasma concentration (Cmax), but the area under the concentration vs time curve to the last
quantifiable concentration (AUClast) was similar in both fed and fasted states. The small decrease in the post-prandial AUClast appeared to
be attributable to the corresponding increase in the terminal elimination rate constant under the fed conditions. The time to Cmax (Tmax)
was more variable in the fasted state, ranging from 1.5 to 8 hours compared to 2 to 6 hours for the fed state. The elimination half-life (t ½) was also more variable in the fasted state, ranging from 3.89 to 10.35 hours compared to 2.98 to 7.81 hours for the fed state.

EFFECTIVENESS:

Effectiveness of PROIN ER was demonstrated in a multi-center, prospective, open-label, 6-month study in client-owned dogs of various breeds. In this study, 119 dogs (113 spayed females and 6 neutered males, aged 1-16 years and weighing 4.9-81.8 kg) who were considered well controlled for signs of urinary incontinence (UI) while receiving PROIN Chewable Tablets for at least 30 days prior to study start were enrolled in the study. Of these dogs, 104 were evaluated for effectiveness. The owners continued to administer PROIN Chewable Tablets twice a day and recorded episodes of UI during a baseline period (Day -7 through Day -1). After the baseline period, the owners transitioned to administration of PROIN ER once a day, at the labeled dose (see Dosage and Administration), and recorded urinary accidents for 28 days.

The primary variable was the ratio of average daily incidence of UI during the 7 days preceding the Day 28 clinic visit compared to the baseline period. It was concluded that PROIN ER was effective for the control of urinary incontinence due to urethral sphincter hypotonus in dogs.

Table 5: Clinical Effectiveness Results for PROIN ER

Ratio | Number of Dogs N = 104
Ratio >1, indicating response measurement period was better than baseline period | 19 (18.3%)
Ratio of 1, indicating no difference between response measurement period and baseline period | 75 (72.1%)
Ratio <1, indicating response measurement period was worse than baseline period | 10 (9.6%)

The secondary outcome variable was owner assessment of the control of UI at the end of the 28 day study period. The owner assessment was “improved” for 13 (12.5%) dogs, “stayed the same” for 90 (86.5%) dogs and “worsened” for 1 dog (1%).

ANIMAL SAFETY:

The safety of PROIN ER was established based on the safety data from PROIN Chewable Tablets (see below) and a comparative analysis of pharmacokinetic (PK) data for PROIN ER and PROIN Chewable Tablets. The statistical analysis of observed and simulated post-prandial pharmacokinetic data resulted in confidence limits consistent with equal or lower oral bioavailability for PROIN ER when administered once daily versus PROIN Chewable Tablets when administered twice daily. Therefore, the safety data from PROIN Chewable Tablets could be applied to PROIN ER. Emesis and hyperemia of the ventral abdomen were observed during the PK studies.

Target Animal Safety Study (PROIN Chewable Tablets, NADA 141-324)

In a target animal safety study, PROIN was administered to 32 healthy male and female Beagle dogs at 0, 2, 6 and 10 mg/kg of body weight (0, 1, 3, and 5 times the recommended dose; 8 dogs per group) twice daily for 26 consecutive weeks. The most pronounced finding was a dose-dependent increase in blood pressure. Mean systolic blood pressure was increased in all PPA-treated groups compared to the control, but mean values for all 4 groups were within the normal range. Mean diastolic and mean MAP (mean arterial pressure) were higher in the 3X and 5X groups, and in the 1X males. Dogs in the 3X and 5X groups had more individual systolic, diastolic, and MAP values above the normal range than the control group dogs. A dose-dependent decrease in heart rate was observed in the 3X and 5X dogs. In the 0, 1, 3, and 5X groups, 5%, 34%, 44% and 40% of the total number of heart rates obtained from electrocardiograms for each group over the course of the study were below the normal range (70-120 beats per minute), with the lowest value being 51 bpm in 4 of the 1X group dogs. One dog in each of the 1X and 5X had an elevated heart rate between 150-180 beats per minute on at least 2 of the 13 physical exams. One dog in each of the 1X and 3X groups developed gallop heart sounds after treatment began that were noted in 12 of 13 and 6 of 13 physical exams respectively. Dogs in the PPA-treated group exhibited anxious/ restless behavior more frequently than the control group. One dog each in the 1X and 3X were responsible for the majority of the observations. A decline in mean body weight and body condition was observed in females in all 4 groups, including the control. One female in the 1X group lost 33% body weight. Vomiting and loose stool occurred in a dose-related fashion, and most of the vomiting episodes took place within 1 hour of dosing. Mean platelet counts were higher in at least one of the PPA treated groups, with individual values up to 1.4X the upper limit of normal (ULN) in the 3X and 5X group. The 3X and 5X groups had higher mean serum ALT values compared to the control. Mean ALT was within the normal range for all 4 groups. There were more dogs with ALT levels above the normal range in the 3X PPA treated compared to the control, but increased values were transient and less than 1.8X ULN. All dogs had ALT values in the normal range at the conclusion of the study.

Tolerance Study (PROIN Chewable Tablets, NADA 141-324)

In a separate tolerance study, 6 healthy female Beagle dogs were administered PROIN at 20 mg/kg body weight (10 times the recommended dose) twice daily for 21 consecutive days. Mean systolic blood pressure was increased in the 10X group compared to the control, but mean values were within the normal range for both groups. Mean diastolic pressures were above the normal range on days 7 and 21 for the 10X group, and day 14 for the control. The 10X dogs had hypertensive MAP values on days 7 and 21, whereas the control dog mean MAP values were in the normal range. There was a trend in 10X dogs for lower heart rates following initiation of PPA treatment. Four of 6 dogs in the 10X group had heart rates below the normal range on day 7, whereas none of the control dogs did. The 10X group dogs had increased hematocrit, hemoglobin, RBC counts, urine specific gravity, and water intake consistent with transient, sub-clinical dehydration that occurred shortly after PPA treatment was started. All 6 dogs in the 10X group vomited at least once during the treatment period, whereas only 1 of the control dogs did. Most of the vomiting episodes took place within 1 hour of dosing. Mean platelet counts were also higher in the 10X dogs on all 3 exam days; mean values were above the normal range on day 7, with individual values up to 1.5X ULN. The 10X group had a higher mean serum ALT value on day 7 than the control. Mean ALT values for both groups were in the normal range on all 3 exam days, but 2 dogs in the 10X group had ALT values up to 1.4X ULN on day 7; these elevated values were transient, and all dogs had normal ALT values on days 14 and 21.

For either study, there was no evidence of chronic hypertension-induced target organ damage; there were no clinical findings attributed to PPA on the ophthalmic exams, electrocardiogram evaluation, or gross necropsy and histopathology.

STORAGE:

Store at controlled room temperature 20-25°C (68-77°F), excursions permitted between 15-40°C (59-104°F)

HOW SUPPLIED:

PROIN ER tablets contain 18, 38, 74 or 145 mg phenylpropanolamine hydrochloride per tablet. PROIN ER is packaged in bottles containing 30 or 90 tablets.

REFERENCES:

^1 Watson R, et. al. Ephedra alkaloids inhibit platelet aggregation. Blood Coagulation and Fibrinolysis. 2010 21: 266-271

^2 Richter K. P., Ling G.V. Clinical response and urethral pressure profile changes after phenylpropanolamine in dogs with primary sphincter incompetence. JAVMA Vol 187 No. 6, September 15, 1985, 605-611.

^3 Scott, L., Leddy M., and Bernay F. Evaluation of phenylpropanolamine in the treatment of urethral sphincter mechanism incompetence in the bitch. J. Small Animal Pract. 2002; 43 (11): 493-6.

^4 Noel, S., et. al. Combined pharmacokinetic and urodynamic study of the effects of oral administration of phenylpropanolamine in female Beagle dogs. Vet Journal, 2010; 184 (2): 201-207.

Approved by FDA under NADA #141-517

PROIN ER is a trademark of Pegasus Laboratories, Inc.

04/2023

Manufactured By:

Pegasus Laboratories, Inc.

Employee-Owned

Pensacola, FL 32514, USA

Principal Display Panel

PROIN ER™

(phneyl propanolamine hydrochloride extended-release tablets)

145 mg / for dogs 81 -125 ilbs of body weight

For oral use in dogs only

Caution: Federal law restrics this drug to use by or on the order of a licensed veterinarian.

Sympathomimetic amine drug

Approved by FDA under NADA # 141-517

NDC #: 49427-347-57 or 49427-347-44

PRN Pharmacal

NET CONTENTS 30 or 90 TABLETS

Add image transcription here...

Add image transcription here...